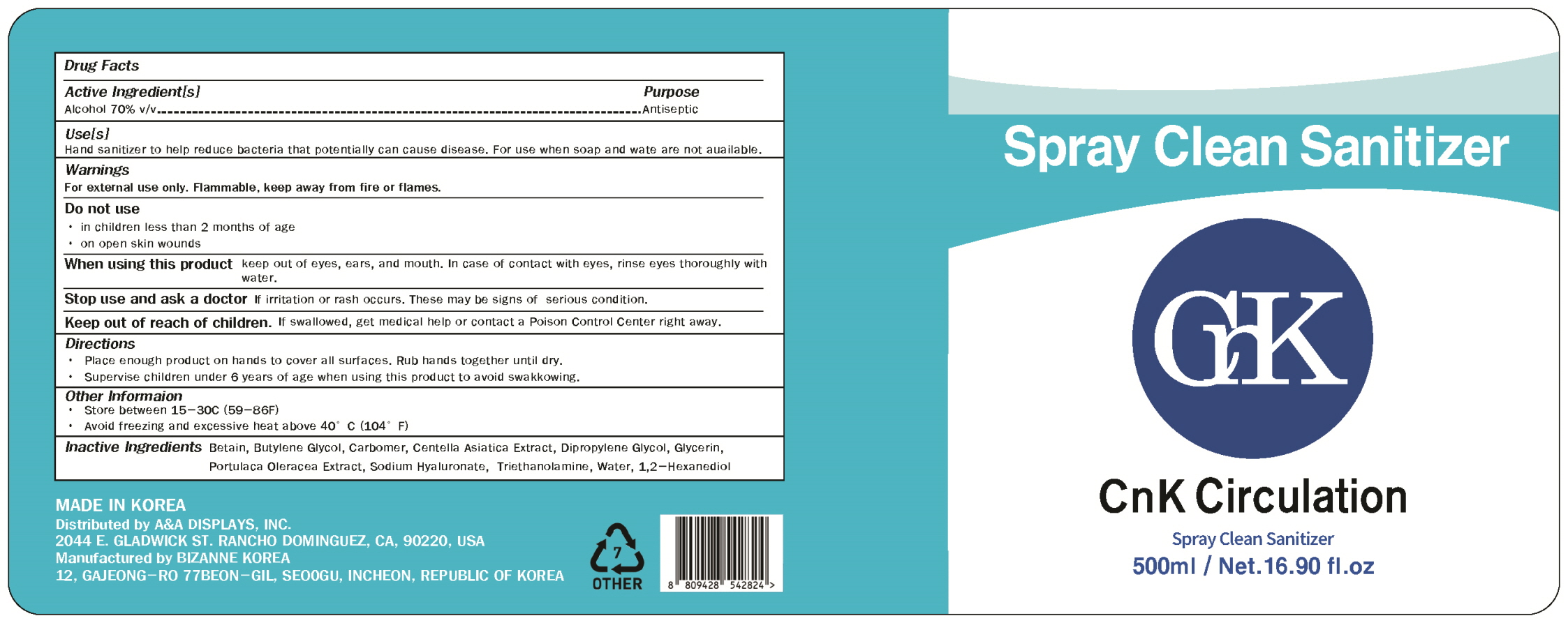 DRUG LABEL: CnK Circulation-Spray Clean Sanitizer (500ml)
NDC: 79274-0004 | Form: LIQUID
Manufacturer: Bizanne Korea
Category: otc | Type: HUMAN OTC DRUG LABEL
Date: 20200818

ACTIVE INGREDIENTS: ALCOHOL 350 mL/500 mL
INACTIVE INGREDIENTS: WATER; TROLAMINE; CARBOMER HOMOPOLYMER, UNSPECIFIED TYPE; GLYCERIN; BUTYLENE GLYCOL; CENTELLA ASIATICA; DIPROPYLENE GLYCOL; HYALURONATE SODIUM; PURSLANE; 1,2-HEXANEDIOL; BETAINE

Bizanne Korea - CnK Circulation Spray Clean Sanitizer (500ml)

ACTIVE INGREDIENT

Alcohol

INACTIVE INGREDIENT

1,2-hexanediol, betaine, butylene glycol, carbomer, centella asiatica extract, dipropylene glycol, glycerin, portulaca oleracea extract, sodium hyaluronate, triethanolamine, water,

PURPOSE

Antiseptic

keep out of reach of the children

INDICATIONS AND USAGE

Please enough product on hands to cover all surfaces. Rub hands together until dry.

Supervise children under 6 years of age when using this product to avoid swakkkowing.

WARNINGS

For external use only. Flammable, keep away from fire or flames.

Do not use

- in children less than 2 months of age
- on open skin wounds

When using this product keep out of eyes, ears, and mouth. In case of contact with eyes, rinse eyes thoroughly with water.

Stop use and ask a doctor if irritation or rash occurs. These may be signs of serious condition.

Keep out of reach of children. If swallowed, get medical help or contact a Poison Control Center right away.

DOSAGE AND ADMINISTRATION

for external use only